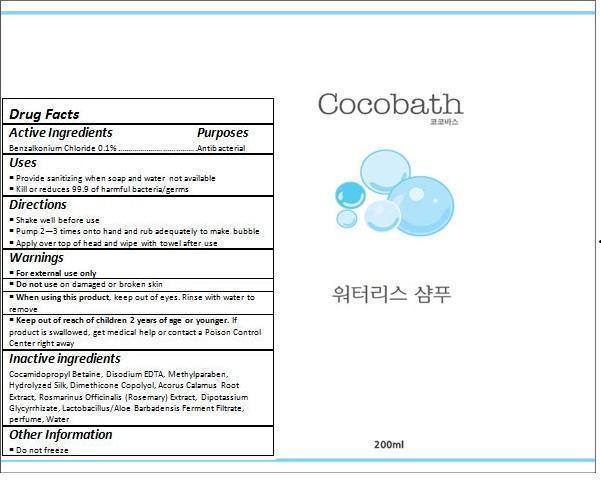 DRUG LABEL: Cocobath Waterless
NDC: 70072-001 | Form: SHAMPOO
Manufacturer: giod Co.
Category: otc | Type: HUMAN OTC DRUG LABEL
Date: 20150905

ACTIVE INGREDIENTS: BENZALKONIUM CHLORIDE 0.19 g/191.64 g
INACTIVE INGREDIENTS: COCAMIDOPROPYL BETAINE; EDETATE DISODIUM; METHYLPARABEN; BOMBYX MORI FIBER; ACORUS CALAMUS ROOT; ROSEMARY; GLYCYRRHIZINATE DIPOTASSIUM; WATER

Drug Facts

ACTIVE INGREDIENT

Benzalkonium Chloride 0.1%

PURPOSE

Antibacterial

INDICATIONS AND USAGE

Provide sanitizing when soap and water not available
Kill or reduces 99.9 of harmful bacteria/germs

DOSAGE AND ADMINISTRATION

Pump 2—3 times onto hand and rub adequately to make bubble
Apply over top of head and wipe with towel after use

WARNINGS

For external use only.
Do not use on damaged or broken skin.
When using this product, keep out of eyes. Rinse with water to remove.
Stop using and ask a doctor if rash occurs.

KEEP OUT OF REACH OF CHILDREN

Keep out of reach of the children. If product is swallowed, get medical help or contact a poison control center right away.

INACTIVE INGREDIENT

Cocamidopropyl Betaine, Disodium EDTA, Methylparaben, Hydrolyzed Silk, Dimethicone Copolyol, Acorus Calamus Root Extract, Rosmarinus Officinalis (Rosemary) Extract, Dipotassium Glycyrrhizate, Lactobacillus/Aloe Barbadensis Ferment Filtrate, perfume, Water